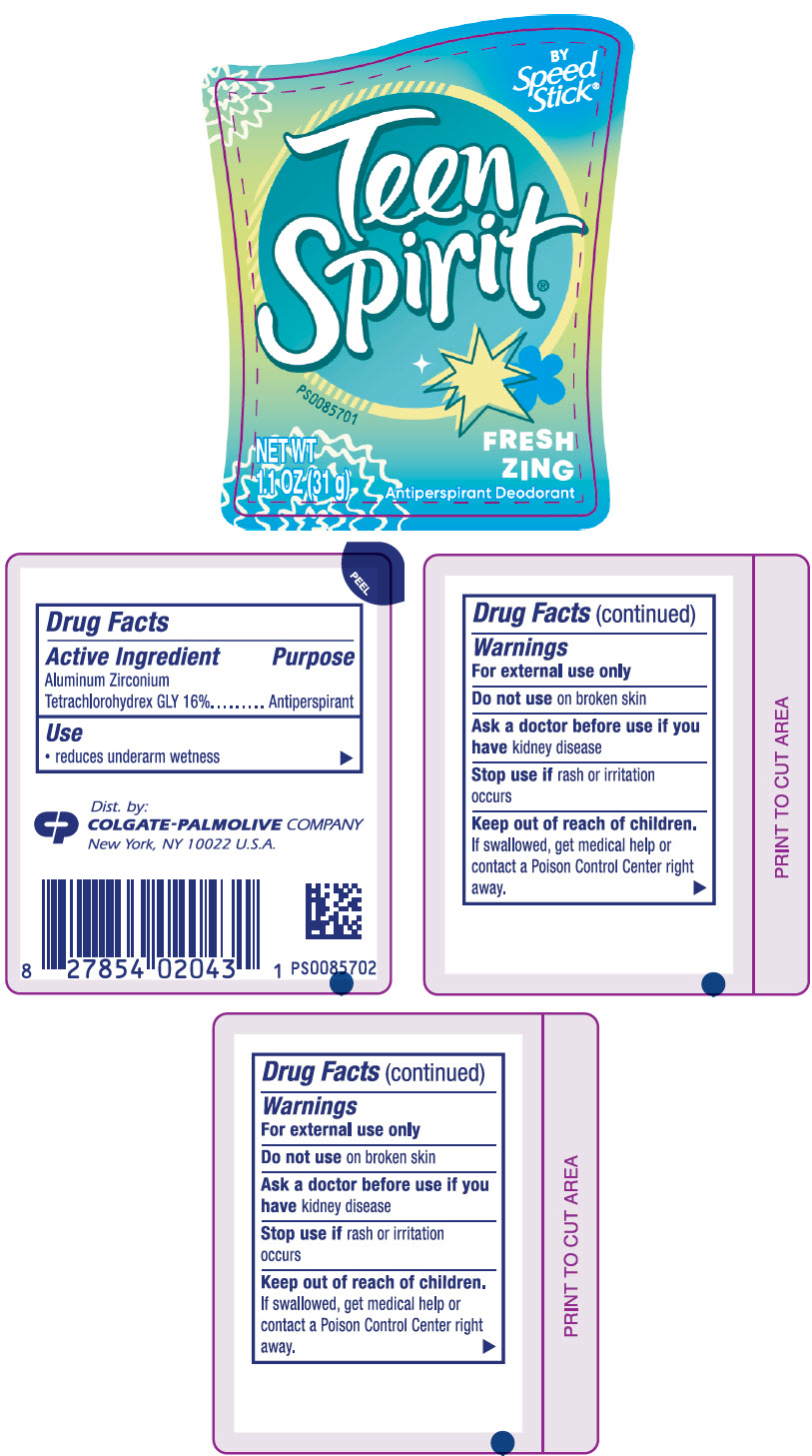 DRUG LABEL: Ladies Speed Stick
NDC: 35000-659 | Form: STICK
Manufacturer: Colgate-Palmolive Company
Category: otc | Type: HUMAN OTC DRUG LABEL
Date: 20250717

ACTIVE INGREDIENTS: ALUMINUM ZIRCONIUM TETRACHLOROHYDREX GLY 160 mg/1 g
INACTIVE INGREDIENTS: PALM KERNEL OIL; STEARYL ALCOHOL; CYCLOMETHICONE 5; ALKYL (C12-15) BENZOATE; PPG-14 BUTYL ETHER; HYDROGENATED CASTOR OIL; HYDROGENATED SOYBEAN OIL; PEG-8 DISTEARATE; DOCOSANOL; ANHYDROUS CITRIC ACID; PENTAERYTHRITOL TETRAKIS(3-(3,5-DI-TERT-BUTYL-4-HYDROXYPHENYL)PROPIONATE)

Ladies Speed Stick®
Teen Spirit® Fresh Zing

Drug Facts

Active Ingredient

Aluminum Zirconium Tetrachlorohydrex GLY 16%

Purpose

Antiperspirant

Use

- reduces underarm wetness

Warnings

For external use only

Do not use on broken skin

Ask a doctor before use if you have kidney disease

Stop use if rash or irritation occurs

Keep out of reach of children.

If swallowed, get medical help or contact a Poison Control Center right away.

Directions

apply to underarms only

Inactive ingredients

Elaeis Guineensis (Palm) Kernel Oil, Stearyl Alcohol, Cyclomethicone, C12-15 Alkyl Benzoate, PPG-14 Butyl Ether, Hydrogenated Castor Oil, Hydrogenated Soybean Oil, PEG-8 Distearate, Fragrance, Behenyl Alcohol, Citric Acid, Pentaerythrityl Tetra-Di-T-Butyl Hydroxyhydrocinnamate.

Questions?

Call 1-800-228-7408

Dist. by:
COLGATE-PALMOLIVE COMPANY
New York, NY 10022 U.S.A.

PRINCIPAL DISPLAY PANEL - 31 g Container Label

BY
Speed
Stick®

Teen
Spirit®

PS0085701

FRESH
ZING

NET WT
1.1 OZ (31 g)

Antiperspirant Deodorant